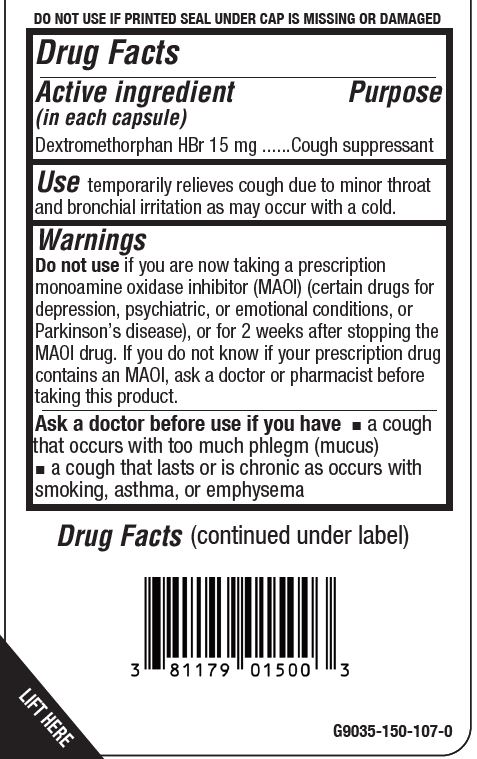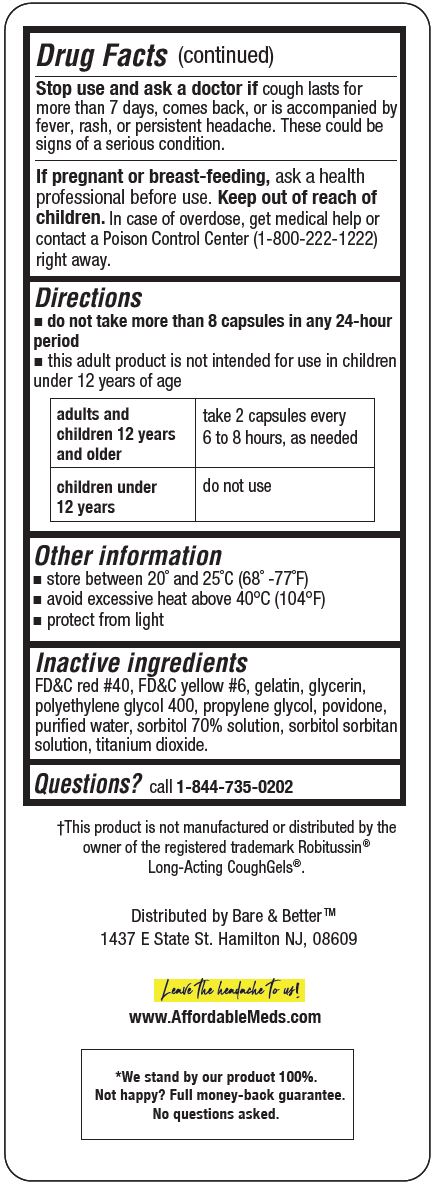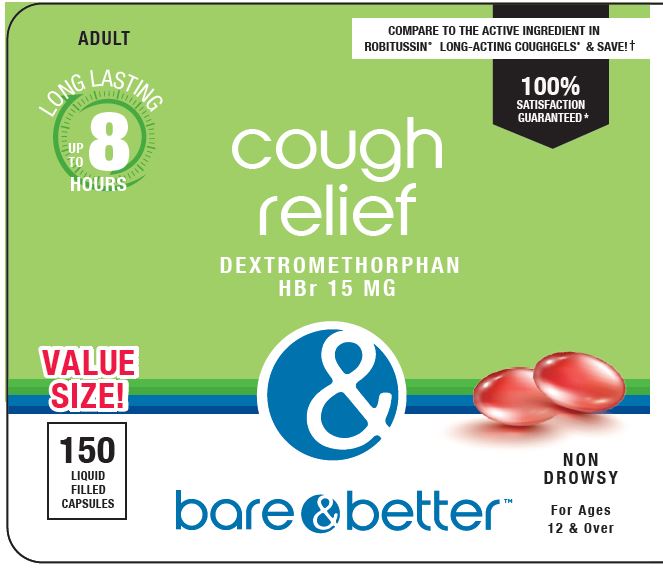 DRUG LABEL: COUGH RELIEF
NDC: 81179-015 | Form: CAPSULE, LIQUID FILLED
Manufacturer: YET HEALTH GROUP LLC
Category: otc | Type: HUMAN OTC DRUG LABEL
Date: 20240103

ACTIVE INGREDIENTS: DEXTROMETHORPHAN HYDROBROMIDE 15 mg/1 1
INACTIVE INGREDIENTS: FD&C RED NO. 40; FD&C YELLOW NO. 6; GELATIN; GLYCERIN; POLYETHYLENE GLYCOL 400; PROPYLENE GLYCOL; POVIDONE; WATER; SORBITOL SOLUTION 70%; SORBITAN; SORBITOL; TITANIUM DIOXIDE

YET - BARE & BETTER COUGH RELIEF - DEXTROMETHORPHAN HBR 15 MG

Active ingredient (in each capsule)

Dextromethorphan HBr 15 mg

Purpose

Cough suppressant

Uses

temporarily relieves cough due to minor throat and bronchial irritation as may occur with a cold.

Warnings

Do not use if you are now taking a prescription monoamine oxidase inhibitor (MAOI) (certain drugs for depression, psychiatric, or emotional conditions, or Parkinson’s disease), or for 2 weeks after stopping the MAOI drug. If you do not know if your prescription drug contains an MAOI, ask a doctor or pharmacist before taking this product.

Ask a doctor before use if you have

- a cough that occurs with too much phlegm (mucus)
- a cough that lasts or is chronic as occurs with smoking, asthma, or emphysema

Stop use and ask a doctor if cough lasts for more than 7 days, comes back, or is accompanied by fever, rash, or persistent headache. These could be signs of a serious condition.

If pregnant or breast-feeding, ask a health professional before use.

Keep out of reach of children. In case of overdose, get medical help or contact a Poison Control Center (1-800-222-1222) right away.

Directions

- do not take more than 8 capsules in any 24-hour period
- this adult product is not intended for use in children under 12 years of age

adults and children 12 years and older | take 2 capsults every 6 to 8 hours, as needed
children under 12 years | do not use

Other information

- store between 20˚ and 25˚C (68˚ -77˚F)
- avoid excessive heat above 40°C (104°F)
- protect from light

Inactive ingredients

FD&C red #40, FD&C yellow #6, gelatin, glycerin, polyethylene glycol 400, propylene glycol, povidone, puriﬁed water, sorbitol 70% solution, sorbitol sorbitan solution, titanium dioxide.

Questions?

call 1-844-735-0202